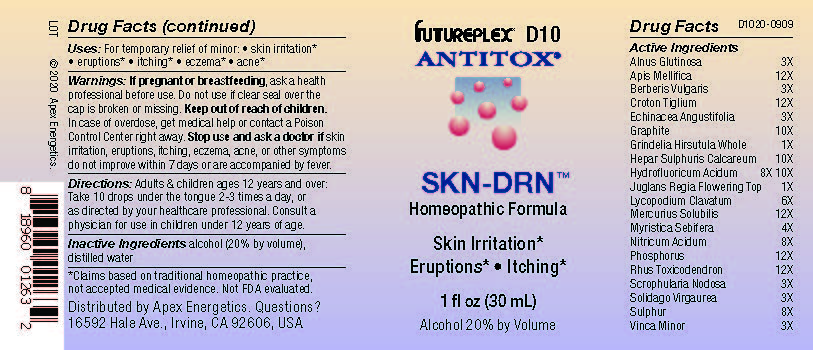 DRUG LABEL: D10
NDC: 63479-0410 | Form: SOLUTION/ DROPS
Manufacturer: Apex Energetics Inc.
Category: homeopathic | Type: HUMAN OTC DRUG LABEL
Date: 20240108

ACTIVE INGREDIENTS: CROTON TIGLIUM SEED 12 [hp_X]/1 mL; ECHINACEA ANGUSTIFOLIA 3 [hp_X]/1 mL; GRAPHITE 10 [hp_X]/1 mL; GRINDELIA HIRSUTULA WHOLE 1 [hp_X]/1 mL; HYDROFLUORIC ACID 10 [hp_X]/1 mL; JUGLANS REGIA FLOWERING TOP 1 [hp_X]/1 mL; VIROLA SEBIFERA RESIN 4 [hp_X]/1 mL; NITRIC ACID 8 [hp_X]/1 mL; PHOSPHORUS 12 [hp_X]/1 mL; TOXICODENDRON PUBESCENS LEAF 12 [hp_X]/1 mL; VINCA MINOR 3 [hp_X]/1 mL; APIS MELLIFERA 12 [hp_X]/1 mL; BERBERIS VULGARIS ROOT BARK 3 [hp_X]/1 mL; CALCIUM SULFIDE 10 [hp_X]/1 mL; LYCOPODIUM CLAVATUM SPORE 6 [hp_X]/1 mL; MERCURIUS SOLUBILIS 12 [hp_X]/1 mL; SCROPHULARIA NODOSA 3 [hp_X]/1 mL; SOLIDAGO VIRGAUREA FLOWERING TOP 3 [hp_X]/1 mL; SULFUR 8 [hp_X]/1 mL; ALNUS GLUTINOSA BARK 3 [hp_X]/1 mL
INACTIVE INGREDIENTS: ALCOHOL; WATER

D10

Active Ingredients
Alnus Glutinosa | 3X
Apis Mellifica | 12X
Berberis Vulgaris | 3X
Croton Tiglium | 12X
Echinacea Angustifolia | 3X
Graphite | 10X
Grindelia Hirsutula Whole | 1X
Hepar Sulphuris Calcareum | 10X
Hydrofluoricum Acidum | 8X 10X
Juglans Regia Flowering Top | 1X
Lycopodium Clavatum | 6X
Mercurius Solubilis | 12X
Myristica Sebifera | 4X
Nitricum Acidum | 8X
Phosphorus | 12X
Rhus Toxicodendron | 12X
Scrophularia Nodosa | 3X
Solidago Virgaurea | 3X
Sulphur | 8X
Vinca Minor | 3X

INDICATIONS AND USAGE

Uses:

For temporary relief of minor:

skin irritation*

eruptions*

itching*

eczema*

acne*

*Claims based on traditional homeopathic practice, not accepted medical evidence. Not FDA evaluated.

Warnings:

PREGNANCY OR BREAST FEEDING

If pregnant or breastfeeding, ask a health professional before use.

Do not use if clear seal over the cap is broken or missing.

Keep out of reach of children. In case of overdose, get medical help or contact a Poison Control Center right away.

Stop use and ask a doctor if skin irritation, eruptions, itching, eczema, acne, or other symptoms do not improve within 7 days or are accompanied by fever.

Directions:

Adults & children ages 12 years and over: Take 10 drops under the tongue 2-3 times a day, or as directed by your healthcare professional. Consult a physician for use in children under 12 years of age.

Inactive Ingredients

alcohol (20% by volume), distilled water

Distributed by Apex Energetics. Questions?

16592 Hale Ave., Irvine, CA 92606, USA

PACKAGE LABEL

FUTUREPLEX® D10

ANTITOX®

SKN-DRN™

Homeopathic Formula

Skin Irritation*

Eruptions* Itching*

1 fl oz (30 mL)

Alcohol 20% by Volume